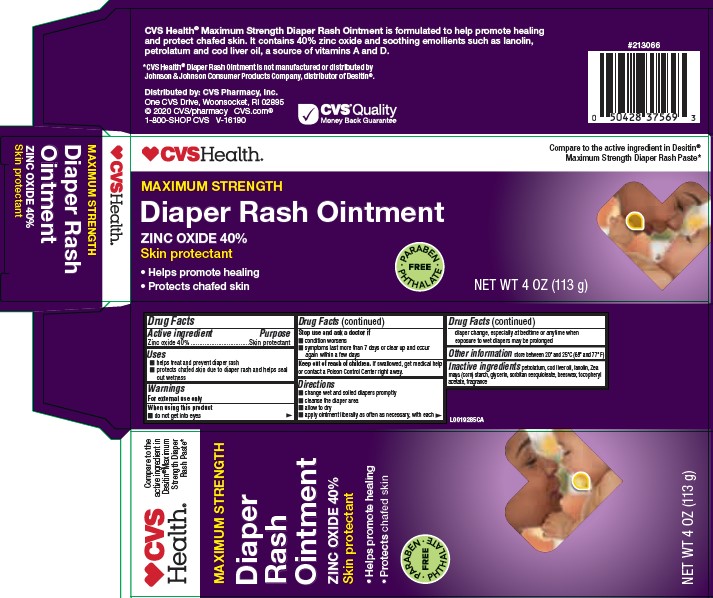 DRUG LABEL: Zinc Oxide
NDC: 69842-468 | Form: PASTE
Manufacturer: CVS Pharmacy, Inc.
Category: otc | Type: HUMAN OTC DRUG LABEL
Date: 20260202

ACTIVE INGREDIENTS: ZINC OXIDE 400 mg/1 g
INACTIVE INGREDIENTS: PETROLATUM; COD LIVER OIL; LANOLIN; STARCH, CORN; GLYCERIN; SORBITAN SESQUIOLEATE; YELLOW WAX; TOCOPHEROL

CVS 020.002/020AC/AD
Diaper Rash Paste

Active ingredient

Zinc oxide 40%

Purpose

Skin Protectant

Uses

- helps treat and prevent diaper rash
- protects chafed skin due to the diaper rash and helps seal out wetness

Warnings

For external use only

When using this product

- do not get into eyes

Stop use and ask a doctor if

- condition worsens
- symptoms last more than 7 days or clear up and occur again within a few days

Keep out of reach of children.

If swallowed, get medical help or contact a Poison Control Center right away.

Directions

- change wet and soiled diapers promptly
- cleanse the diaper area
- allow to dry
- apply ointment liberally as often as necessary, with each diaper change, especially at bedtime or anytime when exposure to wet diapers may be prolonged

Other information

- store between 20⁰ and 25⁰C (68⁰ and 77⁰F)

Inactive ingredients

petrolatum, cod liver oil, lanolin, Zea mays (corn) starch, glycerin, sorbitan sesquioleate, beeswax, tocopheryl acetate, fragrance

Claim

CVS HealthMaximum Strength Diaper Rash Ointment is formulated to help promote healing and protect chafed skin. It contains 40% zinc oxide and soothing emollients such as lanolin, petrolatum and cod liver oil, a source of vitamins A and D.

Disclaimer

*CVS Health®Diaper Rash Ointment is not manufactured or distributed by Johnson & Johnson Consumer Products Company, distributor Desitin.

ADVERSE REACTION

Distributed by: CVS Pharmacy, Inc.

One CVS Drive, Woonsocket, RI 02895

© 2020 CVS/pharmacy CVS.com

1-800-SHOP CVS V-16190

CVSQuality Money Back Guarantee

principal display panel

CVS Health®

Compare to the active ingredient in Desitin®Maximum Strength Diaper Rash Paste*

MAXIMUM STRENGTH

Diaper Rash Ointment

ZINC OXIDE 40%

Skin protectant

- Helps promote healing
- Protects chafed skin

PARABEN - PHTHALATE FREE

NET WT 4 OZ (113 g)